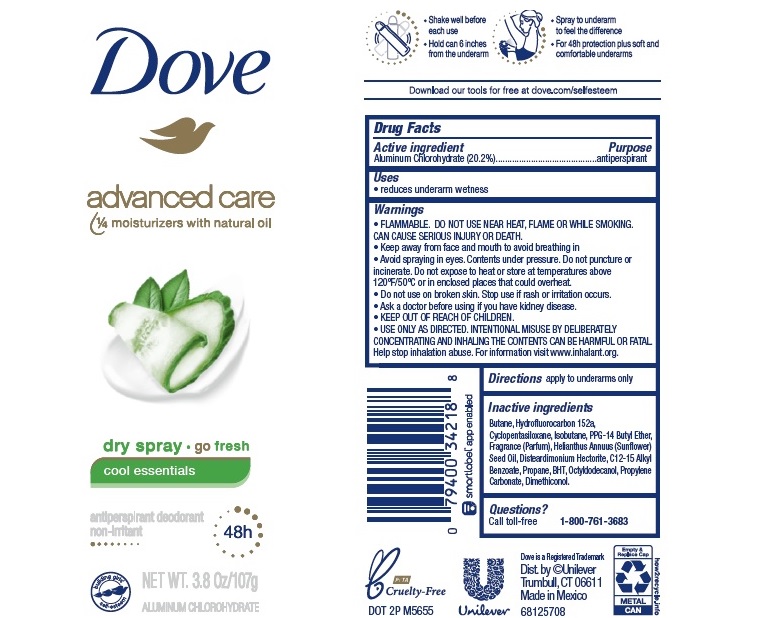 DRUG LABEL: Dove
NDC: 64942-1732 | Form: AEROSOL, SPRAY
Manufacturer: Conopco, Inc. d/b/a Unilever
Category: otc | Type: HUMAN OTC DRUG LABEL
Date: 20241110

ACTIVE INGREDIENTS: ALUMINUM CHLOROHYDRATE 20.2 g/100 g
INACTIVE INGREDIENTS: CYCLOMETHICONE 5; PPG-14 BUTYL ETHER; BUTANE; 1,1-DIFLUOROETHANE; ISOBUTANE; SUNFLOWER OIL; DISTEARDIMONIUM HECTORITE; ALKYL (C12-15) BENZOATE; PROPANE; BUTYLATED HYDROXYTOLUENE; OCTYLDODECANOL; PROPYLENE CARBONATE; DIMETHICONOL (40 CST)

Dove Advanced Care Dry Spray Go Fresh Cool Essentials 48h Antiperspirant Deodorant

DOVE ADVANCED CARE DRY SPRAY GO FRESH COOL ESSENTIALS 48H ANTIPERSPIRANT DEODORANT - aluminum chlorohydrate aerosol, spray

Dove Advanced Care Dry Spray Go Fresh Cool Essentials 48h Antiperspirant Deodorant

Drug Facts

Active ingredient

Aluminum Chlorohydrate (20.2%)

Purpose

antiperspirant

Uses

reduces underarm wetness

Warnings

• FLAMMABLE. DO NOT USE NEAR HEAT, FLAME, OR WHILE SMOKING. CAN CAUSE SERIOUS INJURY OR DEATH
• Keep away from face and mouth to avoid breathing in.
• Avoid spraying in eyes. Contents under pressure. Do not puncture or incinerate. Do not expose to heat or store at temperatures above 120°F/50°C or in enclosed places that could overheat
• Do not use on broken skin. Stop use if rash or irritation occurs.
• Ask a doctor before using if you have kidney disease.
• USE ONLY AS DIRECTED. INTENTIONAL MISUSE BY DELIBERATELY CONCENTRATING AND INHALING THE CONTENTS CAN BE HARMFUL OR FATAL.
Help stop inhalation abuse. For information visit www.inhalant.org

• KEEP OUT OF REACH OF CHILDREN

Directions

apply to underarms only

Inactive ingredients

Butane, Hydrofluorocarbon 152a, Cyclopentasiloxane, Isobutane, PPG-14 Butyl Ether, Fragrance (Parfum), Helianthus Annuus (Sunflower) Seed Oil, Disteardimonium Hectorite, C12-15 Alkyl Benzoate, Propane, BHT, Octyldodecanol, Propylene Carbonate, Dimethiconol.

Questions?

Call toll-free 1-800-761-3683